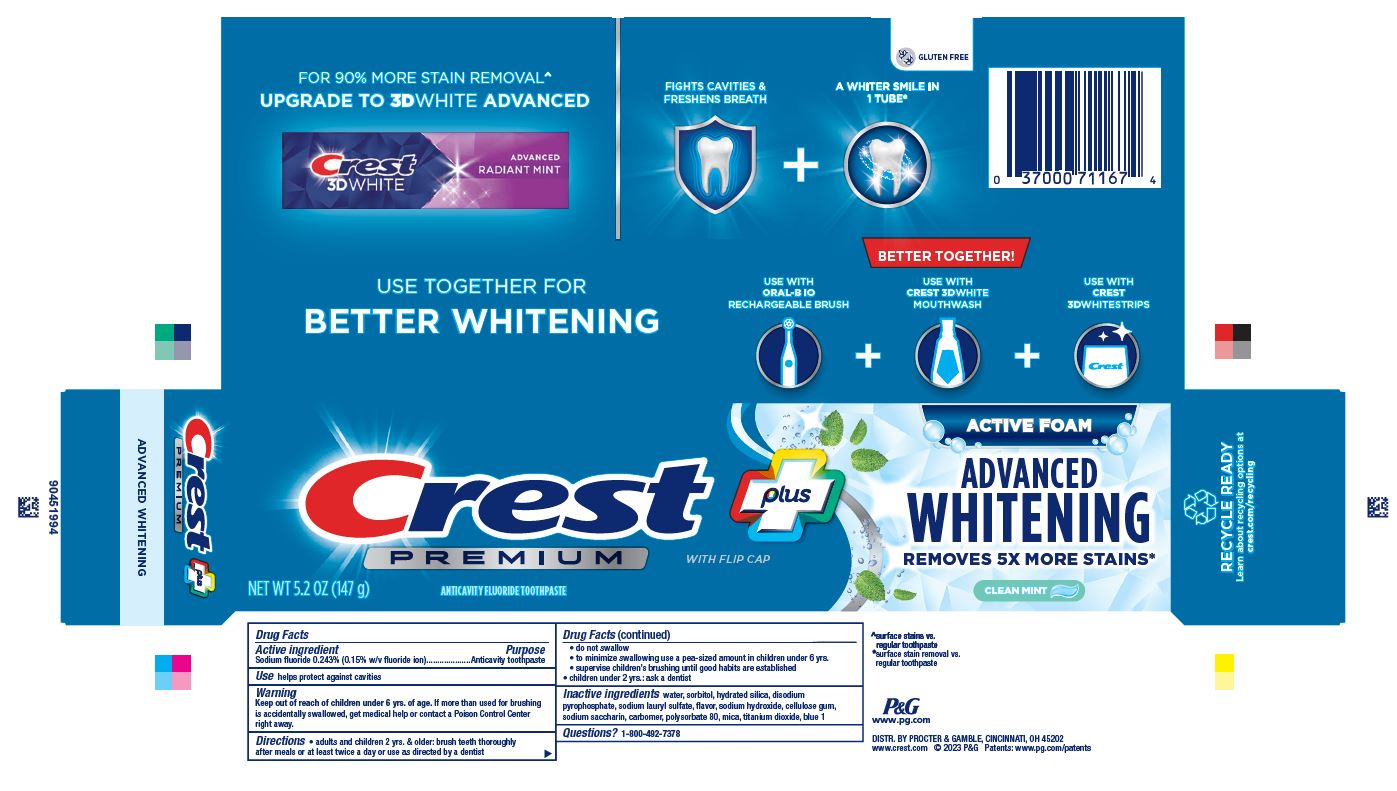 DRUG LABEL: Crest Premium Plus
NDC: 37000-993 | Form: PASTE, DENTIFRICE
Manufacturer: The Procter & Gamble Manufacturing Company
Category: otc | Type: HUMAN OTC DRUG LABEL
Date: 20250820

ACTIVE INGREDIENTS: SODIUM FLUORIDE 1.5 mg/1 g
INACTIVE INGREDIENTS: SODIUM LAURYL SULFATE; CARBOXYMETHYLCELLULOSE SODIUM, UNSPECIFIED FORM; SODIUM HYDROXIDE; SACCHARIN SODIUM; MICA; TITANIUM DIOXIDE; FD&C BLUE NO. 1; POLYSORBATE 80; WATER; SORBITOL; SODIUM ACID PYROPHOSPHATE; HYDRATED SILICA; CARBOXYPOLYMETHYLENE

Crest Premium Plus Advanced Whitening Active Foam

Drug Facts

Active ingredient

Sodium fluoride 0.243% (0.15% w/v fluoride ion)

Purpose

Anticavity toothpaste

Use

helps protect against cavities

Warning

Keep out of reach of children under 6 yrs. of age. If more than used for brushing is accidentally swallowed, get medical help or contact a Poison Control Center right away.

Directions

- adults and children 2 yrs. & older: brush teeth thoroughly after meals or at least twice a day or use as directed by a dentist
- do not swallow
- to minimize swallowing use a pea-sized amount in children under 6
  - supervise children's brushing until good habits are established
- children under 2 yrs.: ask a dentist

Inactive ingredients

water, sorbitol, hydrated silica, disodium
pyrophosphate, sodium lauryl sulfate, flavor, sodium hydroxide, cellulose gum,
sodium saccharin, carbomer, polysorbate 80, mica, titanium dioxide, blue 1

Questions?

1-800-492-7378

DISTR. BY PROCTER & GAMBLE, CINCINNATI, OH 45202

PRINCIPAL DISPLAY PANEL - 204 g Tube Carton

Crest plus Premium with flip cap

NET WT 5.2 OZ (147 g)

ANTICAVITY FLUORIDE TOOTHPASTE

ACTIVE FOAM

ADVANCED

WHITENING

REMOVES 5X MORE STAINS

CLEAN MINT